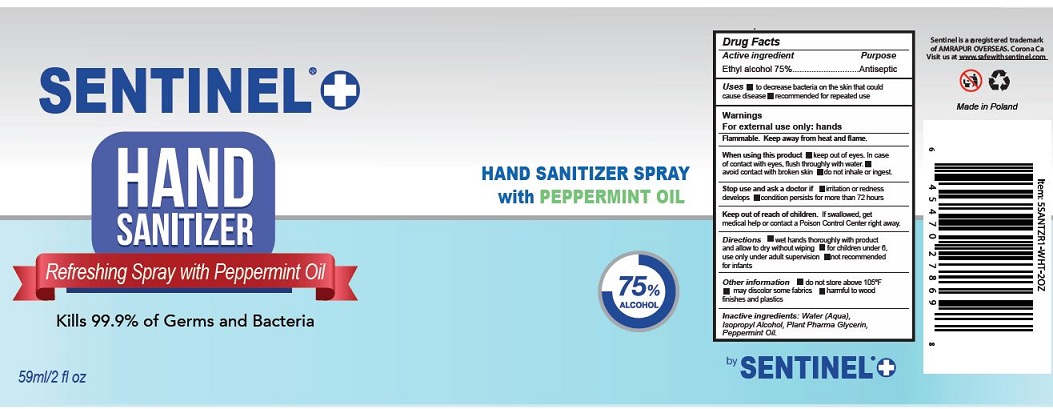 DRUG LABEL: SENTINEL HAND SANITIZER
NDC: 79041-002 | Form: SPRAY
Manufacturer: DANLAB DANUTA KATRYNSKA
Category: otc | Type: HUMAN OTC DRUG LABEL
Date: 20200618

ACTIVE INGREDIENTS: ALCOHOL 75 mL/100 mL
INACTIVE INGREDIENTS: WATER; ISOPROPYL ALCOHOL; GLYCERIN; PEPPERMINT OIL

Active Ingredient

Ethyl Alcohol 75% v/v.

Purpose

Antiseptic

Use

- To decrease bacteria on the skin that coucld cause disease.
- Recommended for repeated use.

Warnings

For external use only:hands.

Flammable. Keep away from heat or flame.

When using this product

- keep out of eyes. In case of contact with eyes, flush thoroughly with water.
- Avoid contact with broken skin.
- Do not inhale or ingest.
- Stop use and ask a doctor if
- irritation or redness develops.
- Condition persists for more than 72 hours.

Keep out of reach of children. If swallowed, get medical help or contact a Poison Control Center right away.

Directions

- Wet hands thoroughly with product and allow to dry without wiping.
- For children under 6, use only under adult supervision.
- Not recommended for infants.

Other information

- Do not store above 105^0F
- May discolor certain fabrics.
- Harmful to wood finishes and plastics

Inactive ingredients

Water (Aqua), Isopropyl alcohol, Plant pharma glycerin, Peppermint oil.